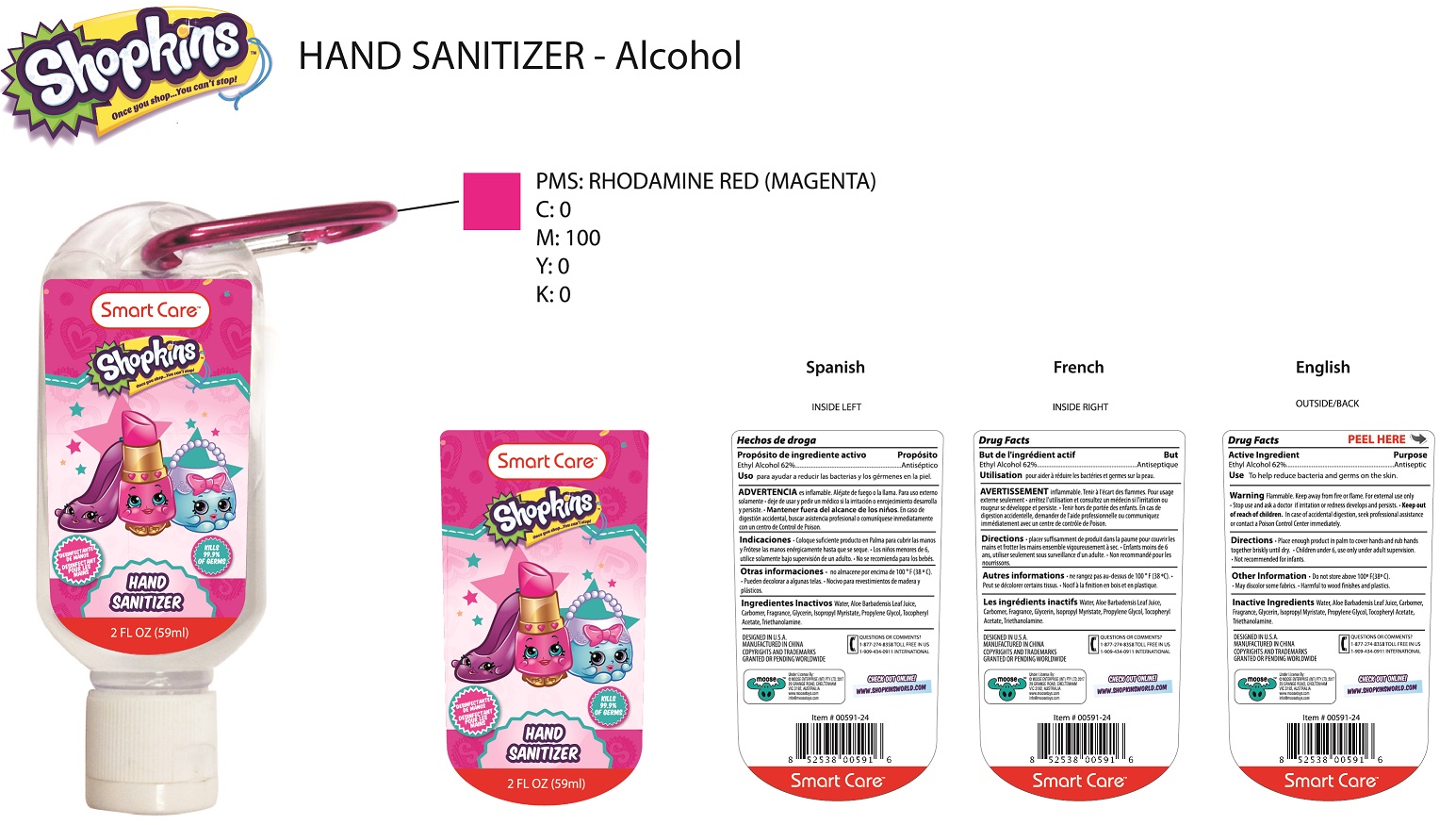 DRUG LABEL: Shopkins hand sanitizer
NDC: 70108-001 | Form: GEL
Manufacturer: Ashtel Studios Inc.
Category: otc | Type: HUMAN OTC DRUG LABEL
Date: 20191231

ACTIVE INGREDIENTS: ALCOHOL 62 g/100 g
INACTIVE INGREDIENTS: ALOE VERA LEAF; CARBOMER COPOLYMER TYPE A (ALLYL PENTAERYTHRITOL CROSSLINKED); GLYCERIN; ISOPROPYL MYRISTATE; PROPYLENE GLYCOL; .ALPHA.-TOCOPHEROL ACETATE; TROLAMINE; WATER

Shopkins hand sanitizer

PURPOSE

To help reduce bacteria and germs on the skin.

Keep out of reach of children. In case of accidental digestion seek professional assistance or contact a poison control center immediately.

INDICATIONS AND USAGE

To help reduce bacteria and germs on the skin.

OTHER SAFETY INFORMATION

Do not store above 100° F(38° C).

May discolor some fabrics. Harmful to wood finishes and Plastics.

WARNINGS

Flammable. Keep away from fire or flame. For external use only. Stop use and ask doctor if irritation or redness develops and persists.

INACTIVE INGREDIENT

Aloe Barbadensis Gel, Carbomer, Fragrance, Glycerin, Isopropyl Myristate, Propylener Glycol, Tococheryl Acetate, Trienthanolamine, Water.

Active Ingredient Purpose

Ethyl Alcohol 62% ......................... Antiseptic

DOSAGE AND ADMINISTRATION

Place enough product in palm to cover hands and rub hands together briskly until dry. Children under 6, use only under adult supervision.
Not recommended for infants.